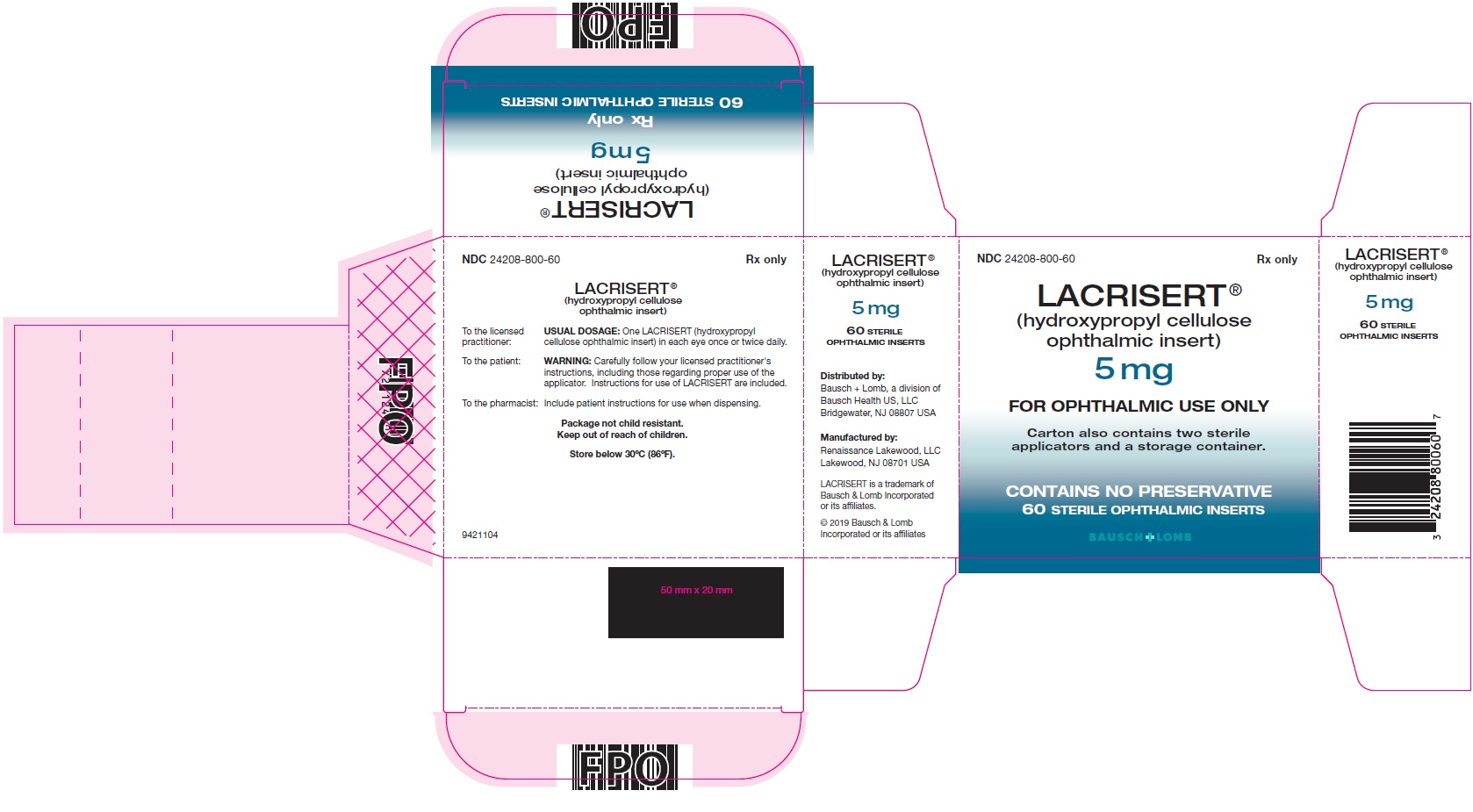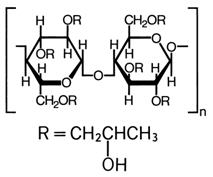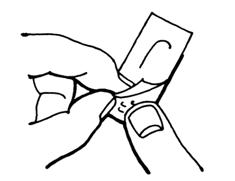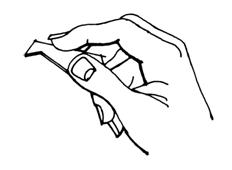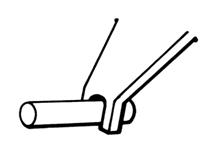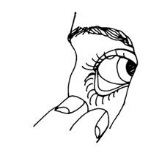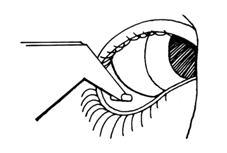 DRUG LABEL: Lacrisert
NDC: 24208-800 | Form: INSERT
Manufacturer: Bausch & Lomb Incorporated
Category: prescription | Type: HUMAN PRESCRIPTION DRUG LABEL
Date: 20240725

ACTIVE INGREDIENTS: HYDROXYPROPYL CELLULOSE (1600000 WAMW) 5 mg/1 1

LACRISERT®(hydroxypropyl cellulose ophthalmic insert)
STERILE OPHTHALMIC INSERT
5 mg

DESCRIPTION

LACRISERT®(hydroxypropyl cellulose ophthalmic insert) is a sterile, translucent, rod-shaped, water soluble, ophthalmic insert made of hydroxypropyl cellulose, for administration into the inferior cul-de-sac of the eye.

The chemical name for hydroxypropyl cellulose is cellulose, 2-hydroxypropyl ether. It is an ether of cellulose in which hydroxypropyl groups (-CH2CHOHCH3) are attached to the hydroxyls present in the anhydroglucose rings of cellulose by ether linkages. A representative structure of the monomer is:

The molecular weight is typically 1 × 10^6.

Hydroxypropyl cellulose is an off-white, odorless, tasteless powder. It is soluble in water below 38°C, and in many polar organic solvents such as ethanol, propylene glycol, dioxane, methanol, isopropyl alcohol (95%), dimethyl sulfoxide, and dimethyl formamide.

Each LACRISERT is 5 mg of hydroxypropyl cellulose. LACRISERT contains no preservatives or other ingredients. It is about 1.27 mm in diameter by about 3.5 mm long.

LACRISERT is supplied in packages of 60 units, together with illustrated instructions and a special applicator for removing LACRISERT from the unit dose blister and inserting it into the eye. A spare applicator is included in each package.

CLINICAL PHARMACOLOGY

Pharmacodynamics

LACRISERT acts to stabilize and thicken the precorneal tear film and prolong the tear film breakup time which is usually accelerated in patients with dry eye states. LACRISERT also acts to lubricate and protect the eye.

LACRISERT usually reduces the signs and symptoms resulting from moderate to severe dry eye syndromes, such as conjunctival hyperemia, corneal and conjunctival staining with rose bengal, exudation, itching, burning, foreign body sensation, smarting, photophobia, dryness and blurred or cloudy vision. Progressive visual deterioration which occurs in some patients may be retarded, halted, or sometimes reversed.

In a multicenter crossover study the 5 mg LACRISERT administered once a day during the waking hours was compared to artificial tears used four or more times daily. There was a prolongation of tear film breakup time and a decrease in foreign body sensation associated with dry eye syndrome in patients during treatment with inserts as compared to artificial tears; these findings were statistically significantly different between the treatment groups. Improvement, as measured by amelioration of symptoms, by slit lamp examination and by rose bengal staining of the cornea and conjunctiva, was greater in most patients with moderate to severe symptoms during treatment with LACRISERT. Patient comfort was usually better with LACRISERT than with artificial tears solution, and most patients preferred LACRISERT.

In most patients treated with LACRISERT for over one year, improvement was observed as evidenced by amelioration of symptoms generally associated with keratoconjunctivitis sicca such as burning, tearing, foreign body sensation, itching, photophobia and blurred or cloudy vision.

During studies in healthy volunteers, a thickened precorneal tear film was usually observed through the slit - lamp while LACRISERT was present in the conjunctival sac.

Pharmacokinetics and Metabolism

Hydroxypropyl cellulose is a physiologically inert substance. In a study of rats fed hydroxypropyl cellulose or unmodified cellulose at levels up to 5% of their diet, it was found that the two were biologically equivalent in that neither was metabolized.

Studies conducted in rats fed^14C-labeled hydroxypropyl cellulose demonstrated that when orally administered, hydroxypropyl cellulose is not absorbed from the gastrointestinal tract and is quantitatively excreted in the feces.

Dissolution studies in rabbits showed that hydroxypropyl cellulose inserts became softer within 1 hour after they were placed in the conjunctival sac. Most of the inserts dissolved completely in 14 to 18 hours; with a single exception, all had disappeared by 24 hours after insertion. Similar dissolution of the inserts was observed during prolonged administration (up to 54 weeks).

INDICATIONS AND USAGE

LACRISERT is indicated in patients with moderate to severe dry eye syndromes, including keratoconjunctivitis sicca. LACRISERT is indicated especially in patients who remain symptomatic after an adequate trial of therapy with artificial tear solutions.

LACRISERT is also indicated for patients with:

- Exposure keratitis
  Decreased corneal sensitivity
  Recurrent corneal erosions

CONTRAINDICATIONS

LACRISERT is contraindicated in patients who are hypersensitive to hydroxypropyl cellulose.

WARNINGS

Instructions for inserting and removing LACRISERT should be carefully followed.

PRECAUTIONS

General

If improperly placed, LACRISERT may result in corneal abrasion (see DOSAGE AND ADMINISTRATION).

Information for Patients

Patients should be advised to follow the instructions for using LACRISERT which accompany the package.

Because this product may produce transient blurring of vision, patients should be instructed to exercise caution when operating hazardous machinery or driving a motor vehicle.

Drug Interactions

Application of hydroxypropyl cellulose ophthalmic inserts to the eyes of unanesthetized rabbits immediately prior to or two hours before instilling pilocarpine, proparacaine HCl (0.5%), or phenylephrine (5%) did not markedly alter the magnitude and/or duration of the miotic, local corneal anesthetic, or mydriatic activity, respectively, of these agents. Under various treatment schedules, the anti-inflammatory effect of ocularly instilled dexamethasone (0.1%) in unanesthetized rabbits with primary uveitis was not affected by the presence of hydroxypropyl cellulose inserts.

Carcinogenesis, Mutagenesis, Impairment of Fertility

Feeding of hydroxypropyl cellulose to rats at levels up to 5% of their diet produced no gross or histopathologic changes or other deleterious effects.

Pediatric Use

Safety and effectiveness in pediatric patients have not been established.

Geriatric Use

No overall differences in safety or effectiveness have been observed between elderly and younger patients.

ADVERSE REACTIONS

The following adverse reactions have been reported in patients treated with LACRISERT, but were in most instances mild and transient:

- Transient blurring of vision (see PRECAUTIONS)
  Ocular discomfort or irritation
  Matting or stickiness of eyelashes
  Photophobia
  Hypersensitivity
  Edema of the eyelids
  Hyperemia

To report SUSPECTED ADVERSE REACTIONS, contact Bausch & Lomb Incorporated at 1-800-321-4576 or FDA at 1-800-FDA-1088 or www.fda.gov/medwatch.

DOSAGE AND ADMINISTRATION

One LACRISERT ophthalmic insert in each eye once daily is usually sufficient to relieve the symptoms associated with moderate to severe dry eye syndromes.

Individual patients may require more flexibility in the use of LACRISERT; some patients may require twice daily use for optimal results.

Clinical experience with LACRISERT indicates that in some patients several weeks may be required before satisfactory improvement of symptoms is achieved.

LACRISERT is inserted into the inferior cul-de-sac of the eye beneath the base of the tarsus, not in apposition to the cornea, nor beneath the eyelid at the level of the tarsal plate. If not properly positioned, it will be expelled into the interpalpebral fissure, and may cause symptoms of a foreign body. Illustrated instructions are included in each package. While in the licensed practitioner's office, the patient should read the instructions, then practice insertion and removal of LACRISERT until proficiency is achieved.

NOTE: Occasionally LACRISERT is inadvertently expelled from the eye, especially in patients with shallow conjunctival fornices. The patient should be cautioned against rubbing the eye(s) containing LACRISERT, especially upon awakening, so as not to dislodge or expel the insert. If required, another LACRISERT ophthalmic insert may be inserted. If experience indicates that transient blurred vision develops in an individual patient, the patient may want to remove LACRISERT a few hours after insertion to avoid this. Another LACRISERT ophthalmic insert may be inserted if needed.

If LACRISERT causes worsening of symptoms, the patient should be instructed to inspect the conjunctival sac to make certain LACRISERT is in the proper location, deep in the inferior cul-de-sac of the eye beneath the base of the tarsus. If these symptoms persist, LACRISERT should be removed and the patient should contact the practitioner.

HOW SUPPLIED

LACRISERT, a sterile, translucent, rod-shaped, water-soluble, ophthalmic insert made of hydroxypropyl cellulose, 5 mg, is supplied as follows:

NDC 24208-800-60 in packages containing 60 unit doses (each wrapped in an aluminum blister), two reusable applicators, and a plastic storage container to store the applicators after use.

Storage

Store below 30°C (86°F).

Distributed by:
Bausch + Lomb, a division of
Bausch Health US, LLC
Bridgewater, NJ 08807 USA

Manufactured by:
Renaissance Lakewood, LLC
Lakewood, NJ 08701 USA

LACRISERT is a trademark of
Bausch & Lomb Incorporated or its affiliates.

© 2019 Bausch & Lomb Incorporated or its affiliates

9421405

Revised: 10/2019

INSTRUCTIONS FOR USE

INSTRUCTIONS FOR USE LACRISERT®(hydroxypropyl cellulose ophthalmic insert) FOR OPHTHALMIC USE ONLY

- Note:
  Your licensed practitioner or a trained associate can demonstrate the proper use of LACRISERT ®. Please read and follow these instructions carefully for your subsequent use.

Clinical experience with LACRISERT indicates that in some patients several weeks may be required before satisfactory improvement of symptoms is achieved.

Two applicators (one spare) are supplied with each package.

Preparing to Insert LACRISERT

Before opening the package of LACRISERT, wash your hands thoroughly with soap and water.

STEP 1:On a flat surface, open blister pocket slowly and smoothly by peeling back label area. Each blister pocket contains one LACRISERT ophthalmic insert.

STEP 2:Open applicator package with label side up. Avoid touching grooved tip of the applicator. Pick up applicator by the wide end and rinse the tip thoroughly under hot running tap water. Gently shake off excess water.

STEP 3:Hold applicator with tip facing down and with forefinger on top to guide and apply gentle pressure. Lightly press the grooved tip of the applicator onto the LACRISERT ophthalmic insert and it will adhere to the applicator.

It is important to follow STEPS 4 and 5 carefully or you might experience difficulty in keeping LACRISERT (hydroxypropyl cellulose ophthalmic insert) in your eye.

STEP 4:Look into a mirror. Starting with the right eye, turn your head to the right so that the colored part of the eye is close to your nose. Use your free hand to grasp the lower lid between the thumb and index finger. Pull the lid away from the eyeball and create a pocket between the white part of the eyeball and the lid.

STEP 5:Place the tip of the applicator containing LACRISERT into the pocket. Avoid touching the colored part of the eye.

Remove the applicator. It is important, after removing the applicator, to look down, then release the lower eyelid. LACRISERT (hydroxypropyl cellulose ophthalmic insert) should remain deep in the lower pocket recess of the eye and not near the edge of the lower eyelid.

Repeat procedure with left eye, turning head to the left so that the colored part of the eye is close to your nose.

Rinse the applicator thoroughly under hot running tap water after use. Gently shake off visible water droplets and promptly return it to the storage container. Note that the storage container provides space for a strip of two LACRISERT ophthalmic inserts next to the applicator storage compartment.

IMPORTANT

If LACRISERT causes worsening of symptoms, or if new symptoms develop, it should be removed and your prescriber contacted.

Should the removal of the LACRISERT ophthalmic insert be necessary, follow these instructions.

1. Locate LACRISERT by pulling the lid away from the eyeball while looking for LACRISERT in a mirror.
2. Then close the eyelids.
3. When located, move LACRISERT upward with your fingers through the closed eyelids.
4. Keep the lids against the eyeball and LACRISERT should slip over the lid margin so that you can remove it with a clean facial tissue without touching the colored part of the eye.

CAUTION:Because this product may produce transient blurring of vision, you should exercise caution when operating hazardous machinery or driving a motor vehicle.

Store below 86°F (30°C)

Distributed by:
Bausch + Lomb, a division of
Bausch Health US, LLC
Bridgewater, NJ 08807 USA

Manufactured by:
Renaissance Lakewood, LLC, Lakewood, NJ
08701 USA

This Instructions for Use has been approved by the U.S. Food and Drug Administration.

LACRISERT is a trademark of
Bausch & Lomb Incorporated or its affiliates.

© 2019 Bausch & Lomb Incorporated or its affiliates

9421304
Revised: 10/2019

PRINCIPAL DISPLAY PANEL - 5 mg Carton of 60

NDC24208-800-60

Rx only

LACRISERT®
(hydroxypropyl cellulose
ophthalmic insert)

5 mg

FOR OPHTHALMIC USE ONLY

Carton also contains two sterile
applicators and a storage container.

CONTAINS NO PRESERVATIVE
60 STERILE OPHTHALMIC INSERTS

BAUSCH + LOMB
9421104